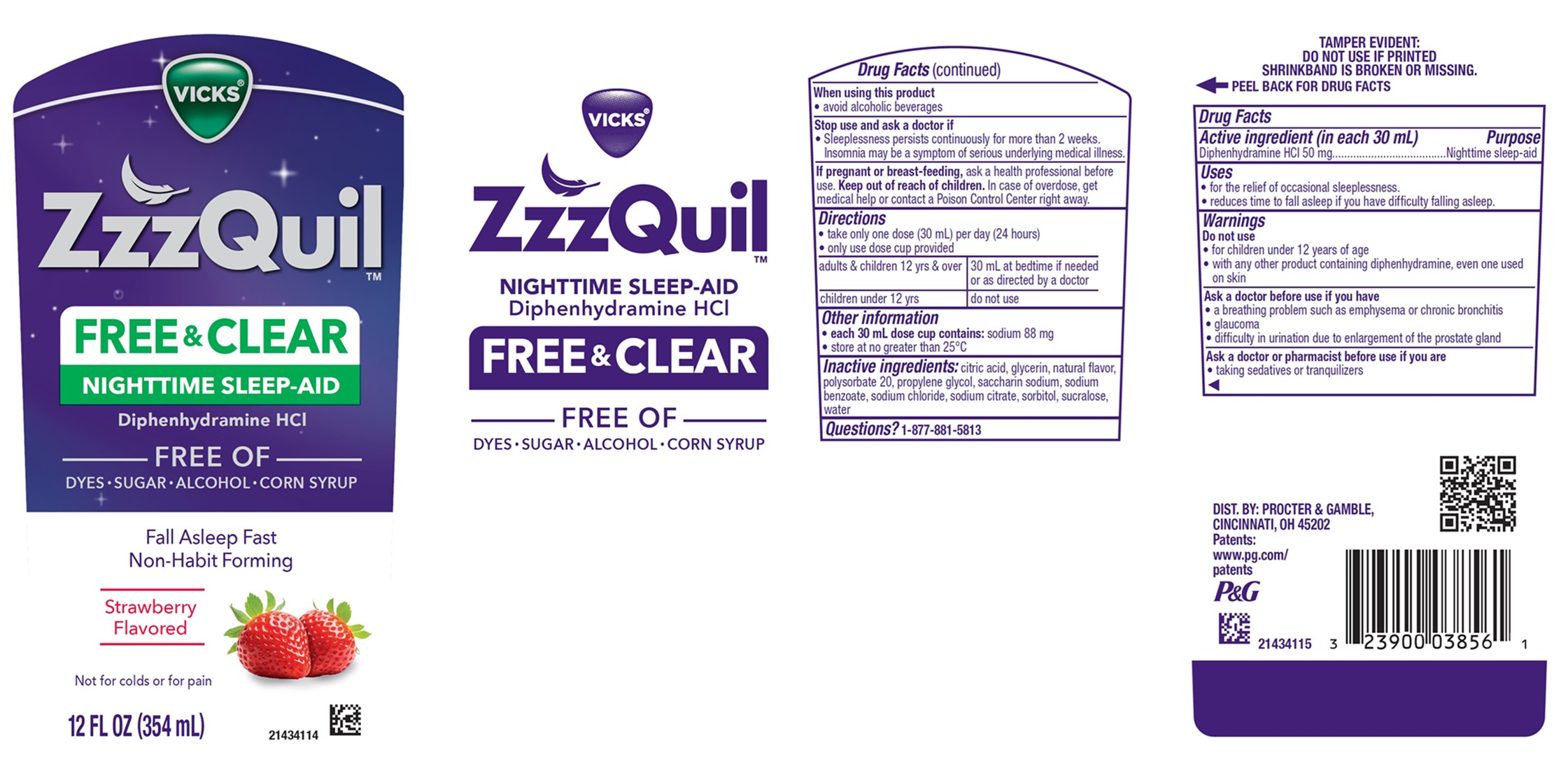 DRUG LABEL: VICKS ZzzQuil FREE and CLEAR
NDC: 84126-370 | Form: LIQUID
Manufacturer: The Procter & Gamble Manufacturing Company
Category: otc | Type: HUMAN OTC DRUG LABEL
Date: 20251222

ACTIVE INGREDIENTS: DIPHENHYDRAMINE HYDROCHLORIDE 50 mg/30 mL
INACTIVE INGREDIENTS: SODIUM CHLORIDE; SODIUM BENZOATE; ANHYDROUS CITRIC ACID; WATER; SACCHARIN SODIUM; GLYCERIN; SORBITOL; SUCRALOSE; TRISODIUM CITRATE DIHYDRATE; POLYSORBATE 20; PROPYLENE GLYCOL

Vicks® ZzzQuil™ FREE & CLEAR NIGHTTIME SLEEP-AID
Diphenhydramine HCl
FREE OF DYES · SUGAR · ALCOHOL · CORN SYRUP
Strawberry Flavored

Drug Facts

Active ingredient (in each 30 mL)

Diphenhydramine HCl 50 mg

Purpose

Nighttime sleep-aid

Uses

- for the relief of occasional sleeplessness.
- reduces time to fall asleep if you have difficulty falling asleep.

Warnings

Do not use

- for children under 12 years of age
- with any other product containing diphenhydramine, even one used on skin

Ask a doctor before use if you have

- a breathing problem such as emphysema or chronic bronchitis
- glaucoma
- difficulty in urination due to enlargement of the prostate gland

Ask a doctor or pharmacist before use if you are

- taking sedatives or tranquilizers

When using this product

- avoid alcoholic beverages

Stop use and ask a doctor if

- sleeplessness persists continuously for more than 2 weeks. Insomnia may be a symptom of a serious underlying medical illness.

If pregnant or breast-feeding,

ask a health professional before use.

Keep out of reach of children.

OVERDOSAGE

In case of overdose, get medical help or contact a Poison Control Center right away.

Directions

- take only one dose (30 mL) per day (24 hours)
- only use dose cup provided

adults & children 12 yrs & over | 30 mL at bedtime if needed or as directed by a doctor
children under 12 yrs | do not use

Other information

- each 30 mL dose cup contains: sodium 88 mg
- store at no greater than 25°C

Inactive ingredients

citric acid, glycerin, natural flavor, polysorbate 20, propylene glycol, saccharin sodium, sodium benzoate, sodium chloride, sodium citrate, sorbitol, sucralose, water

Questions or comments?

1-877-881-5813

TAMPER EVIDENT: DO NOT USE IF PRINTED SHRINKBAND IS BROKEN OR MISSING.

DIST. BY: PROCTER & GAMBLE

CINCINNATI, OH 45202

PRINCIPAL DISPLAY PANEL

Vicks®

ZzzQuil™

FREE & CLEAR

NIGHTTIME SLEEP-AID

Diphenhydramine HCl

FREE OF

DYES · SUGAR · ALCOHOL · CORN SYRUP

Fall Asleep Fast

Non-Habit Forming

Strawberry Flavored

Not for colds or for pain

12 FL OZ (354 mL)